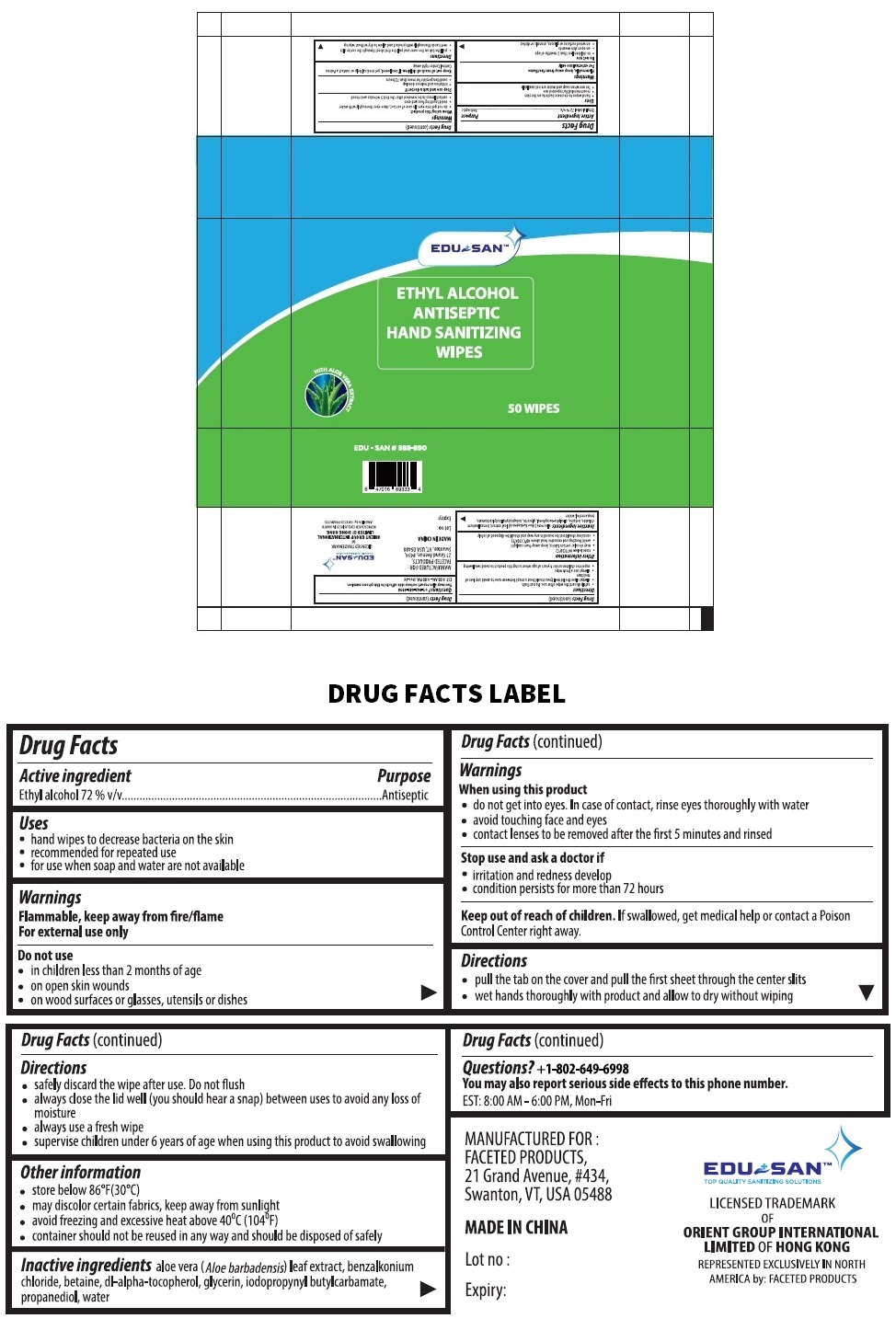 DRUG LABEL: EDU SAN
NDC: 80671-004 | Form: CLOTH
Manufacturer: QUANZHOU AIWINA HYGIENE PRODUCTS CO.,LTD
Category: otc | Type: HUMAN OTC DRUG LABEL
Date: 20210312

ACTIVE INGREDIENTS: ALCOHOL 72 mL/100 mL
INACTIVE INGREDIENTS: ALOE VERA LEAF; BENZALKONIUM CHLORIDE; BETAINE; .ALPHA.-TOCOPHEROL, DL-; GLYCERIN; IODOPROPYNYL BUTYLCARBAMATE; PROPANEDIOL; WATER

EDU + SANTM ETHYL ALCOHOL ANTISEPTIC HAND SANITIZING WIPES

Active ingredient

Ethyl alcohol 72 % v/v

Purpose

Antiseptic

Uses

• hand wipes to decrease bacteria on the skin
• recommended for repeated use
• for use when soap and water are not available

Warnings

Flammable, keep away from fire/flame
For external use only

Do not use

• in children less than 2 months of age
• on open skin wounds
• on wood surfaces or glasses, utensils or dishes

When using this product

• do not get into eyes. In case of contact, rinse eyes thoroughly with water
• avoid touching face and eyes
• contact lenses to be removed after the first 5 minutes and rinsed

Stop use and ask a doctor if

• irritation and redness develop
• condition persists for more than 72 hours

Keep out of reach of children. If swallowed, get medical help or contact a Poison Control Center right away.

Directions

• pull the tab on the cover and pull the first sheet through the center slits

• wet hands thoroughly with product and allow to dry without wiping

• safely discard the wipe after use. Do not flush

• always close the lid well (you should hear a snap) between uses to avoid any loss of moisture

• always use a fresh wipe

• supervise children under 6 years of age when using this product to avoid swallowing

Other information

• store below 86°F(30°C)
• may discolor certain fabrics, keep away from sunlight
• avoid freezing and excessive heat above 40⁰C (104⁰F)
• container should not be reused in any way and should be disposed of safely

Inactive ingredients

aloe vera (Aloe barbadensis) leaf extract, benzalkonium chloride, betaine, dl-alpha-tocopherol, glycerin, iodopropynyl butylcarbamate,
propanediol, water

Questions? +1-802-649-6998

You may also report serious side effects to this phone number.
EST: 8:00 AM - 6:00 PM, Mon-Fri

WITH ALOE VERA EXTRACT

MANUFACTURED FOR :

FACETED PRODUCTS,
21 Grand Avenue, #434,
Swanton, VT, USA 05488

MADE IN CHINA

TOP QUALITY SANITIZING SOLUTIONS

LICENSED TRADEMARK OF ORIENT GROUP INTERNATIONAL LIMITED OF HONG KONG

REPRESENTED EXCLUSIVELY IN NORTH AMERICA by: FACETED PRODUCTS

EDU - SAN # 988-890